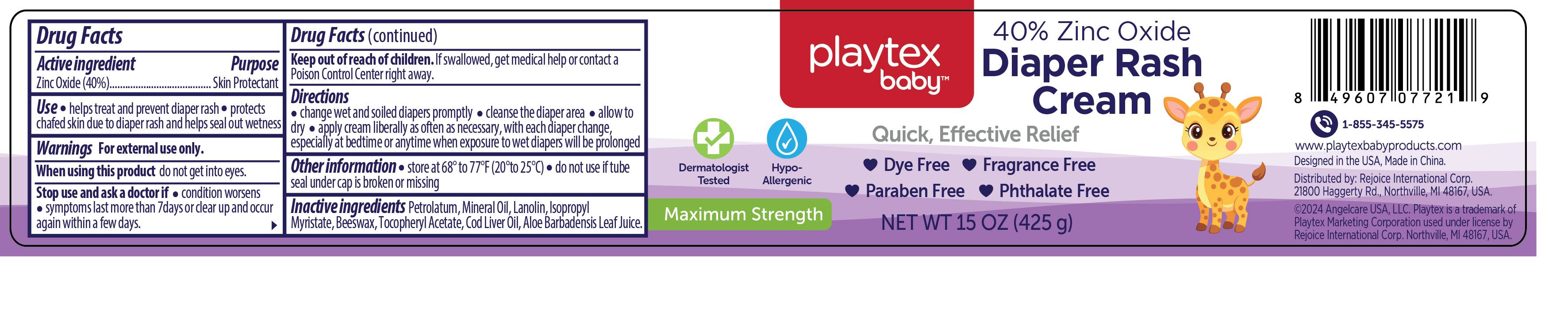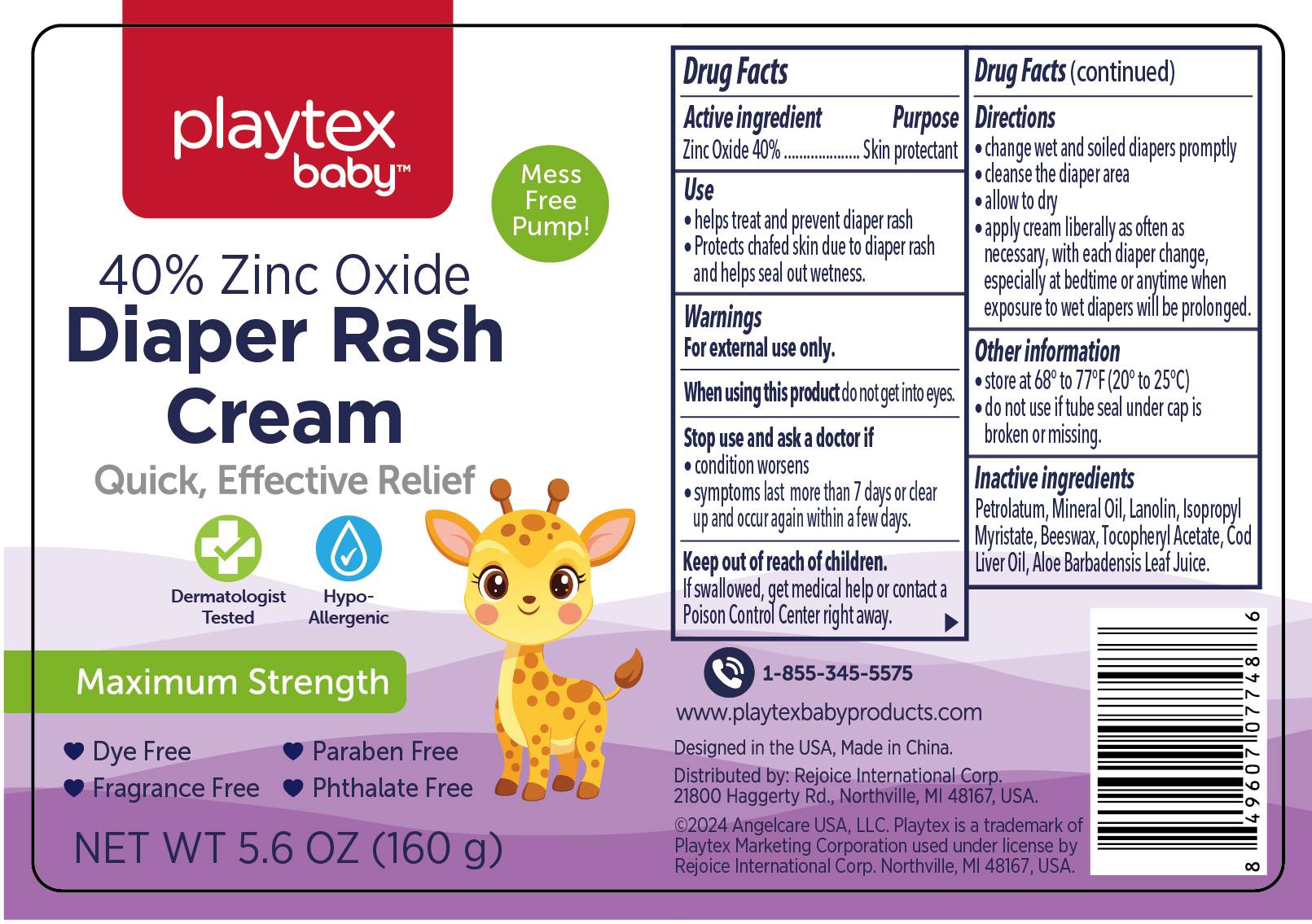 DRUG LABEL: Diaper Rash Cream 15oz
NDC: 58503-205 | Form: CREAM
Manufacturer: China Ningbo Shangge Cosmetics Technology Corp.
Category: otc | Type: HUMAN OTC DRUG LABEL
Date: 20240911

ACTIVE INGREDIENTS: ZINC OXIDE 40 g/100 g
INACTIVE INGREDIENTS: ISOPROPYL MYRISTATE; ALOE VERA LEAF; YELLOW WAX; PETROLATUM; MINERAL OIL; .ALPHA.-TOCOPHEROL ACETATE; LANOLIN; COD LIVER OIL

Active ingredient

Zinc Oxide(40%)

Purpose

Skin Protectant

Use

helps treat and prevent diaper rash
protects chafed skin due to diaper rash and helps seal out wetness

Warnings

For external use only

When using this product do not get into eyes.

Stop use and ask a doctor if

condition worsens
symptoms last more than 7 days or clear up and occur again with a few days.

Keep out of reach of children

If swallowed, get medical help or contact a Poison Control Center right away.

Directions

change wet and soiled diapers promptly
cleanse the diaper area
allow to dry
apply cream liberally as often as necessary, with each diaper change especially at bedtime or anytime when exposure to wet diapers will be prlonged

Other information

store at 68° to 77° F (20° to 25°C)
do not use if tube seal under cap is broken or missing

Inactive ingredients

Petrolatum
Mineral Oil
Lanolin
Isopropyl Myristate
Beeswax
Tocopheryl Acetate
Cod Liver Oil
Aloe Barbadensis Leaf Juice